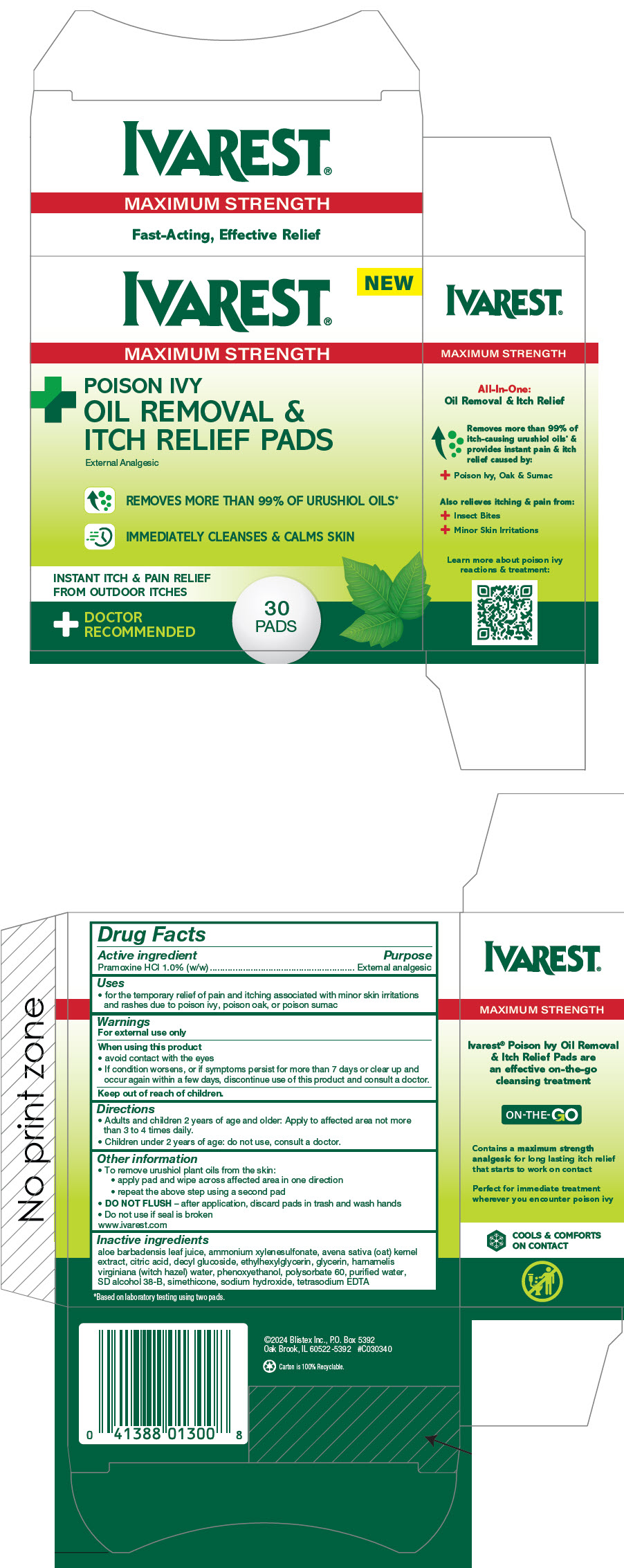 DRUG LABEL: Ivarest Poison Ivy Removal and Itch Relief
NDC: 10157-2125 | Form: LIQUID
Manufacturer: Blistex Inc.
Category: otc | Type: HUMAN OTC DRUG LABEL
Date: 20250429

ACTIVE INGREDIENTS: PRAMOXINE HYDROCHLORIDE 1 g/100 mL
INACTIVE INGREDIENTS: WATER; ALCOHOL; GLYCERIN; OAT; AMMONIUM XYLENESULFONATE; DECYL GLUCOSIDE; HAMAMELIS VIRGINIANA TOP WATER; POLYSORBATE 60; PHENOXYETHANOL; ETHYLHEXYLGLYCERIN; CITRIC ACID MONOHYDRATE; SODIUM HYDROXIDE; EDETATE SODIUM; ALOE VERA LEAF; SILICON DIOXIDE

Ivarest® Poison Ivy Oil Removal and Itch Relief Pads

Drug Facts

Active ingredient

Pramoxine HCl 1.0% (w/w)

Purpose

External analgesic

Uses

- for the temporary relief of pain and itching associated with minor skin irritations and rashes due to poison ivy, poison oak, or poison sumac

Warnings

For external use only

When using this product

- avoid contact with the eyes
- If condition worsens, or if symptoms persist for more than 7 days or clear up and occur again within a few days, discontinue use of this product and consult a doctor.

Keep out of reach of children.

Directions

- Adults and children 2 years of age and older: Apply to affected area not more than 3 to 4 times daily.
- Children under 2 years of age: do not use, consult a doctor.

Other information

- To remove urushiol plant oils from the skin:
  - apply pad and wipe across affected area in one direction
  - repeat the above step using a second pad
- DO NOT FLUSH – after application, discard pads in trash and wash hands
- Do not use if seal is broken

www.ivarest.com

Inactive ingredients

aloe barbadensis leaf juice, ammonium xylenesulfonate, avena sativa (oat) kernel extract, citric acid, decyl glucoside, ethylhexylglycerin, glycerin, hamamelis virginiana (witch hazel) water, phenoxyethanol, polysorbate 60, purified water, SD alcohol 38-B, simethicone, sodium hydroxide, tetrasodium EDTA

PRINCIPAL DISPLAY PANEL - 30 Pad Jar Carton

IVAREST®

NEW

MAXIMUM STRENGTH

+
POISON IVY
OIL REMOVAL &
ITCH RELIEF PADS
External Analgesic

REMOVES MORE THAN 99% OF URUSHIOL OILS*

IMMEDIATELY CLEANSES & CALMS SKIN

INSTANT ITCH & PAIN RELIEF
FROM OUTDOOR ITCHES

+
DOCTOR
RECOMMENDED

30
PADS